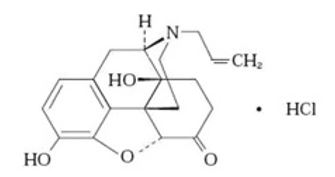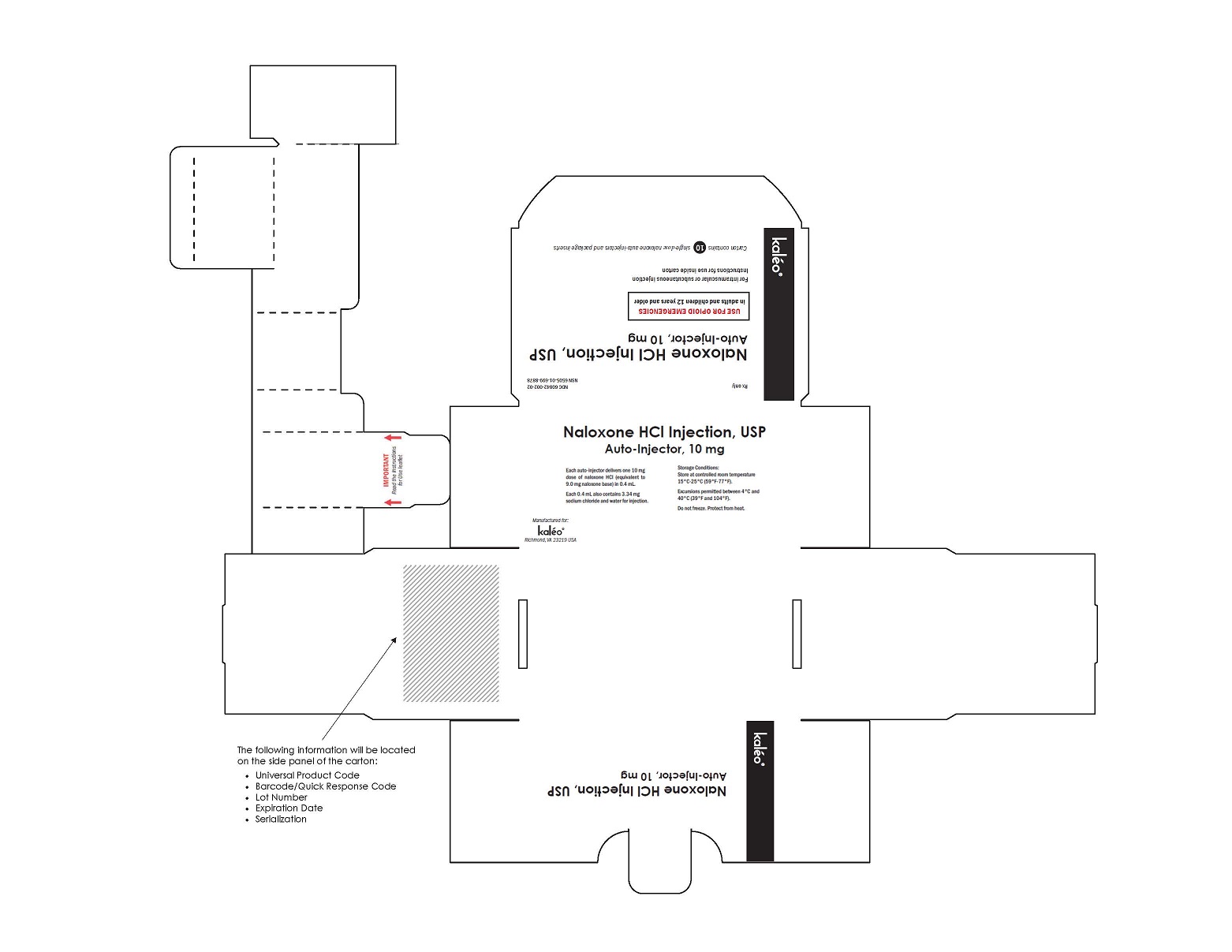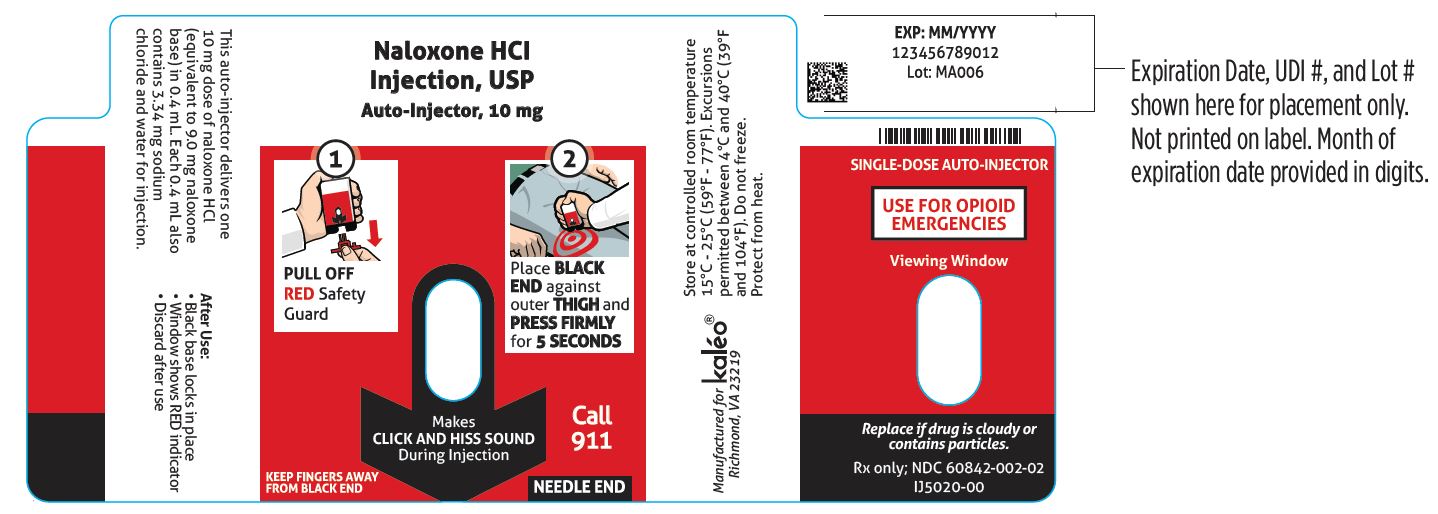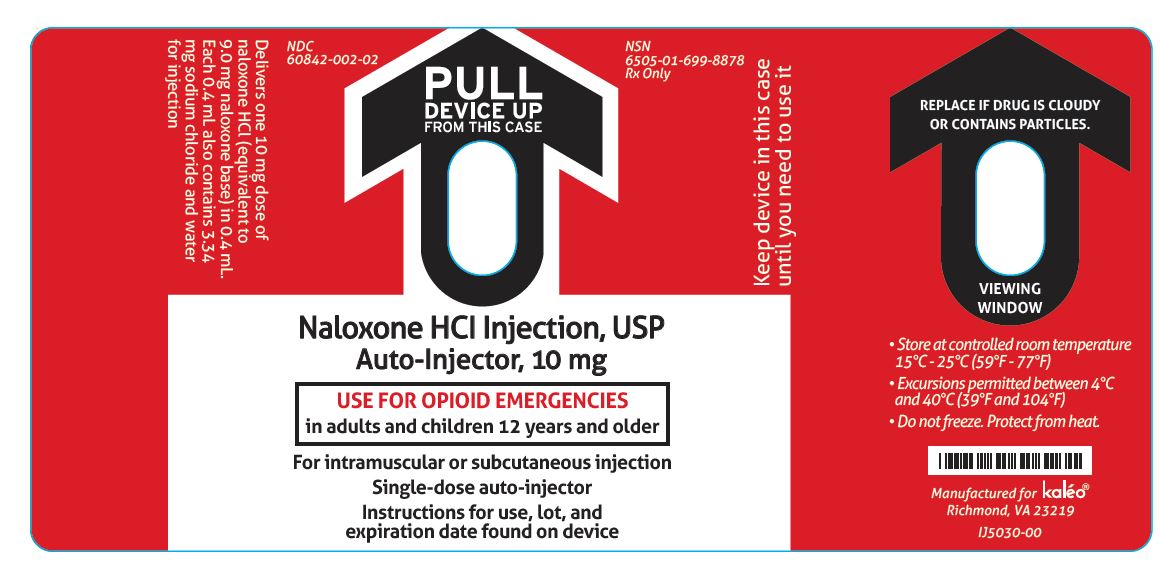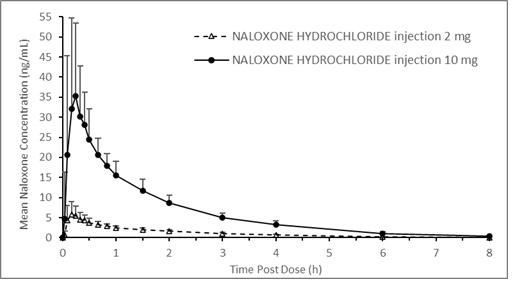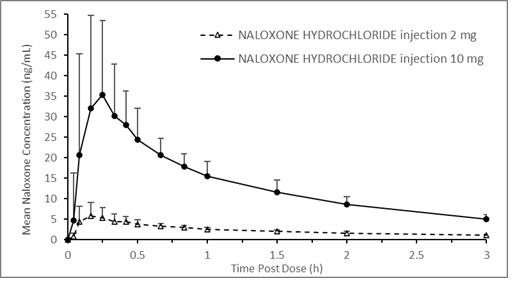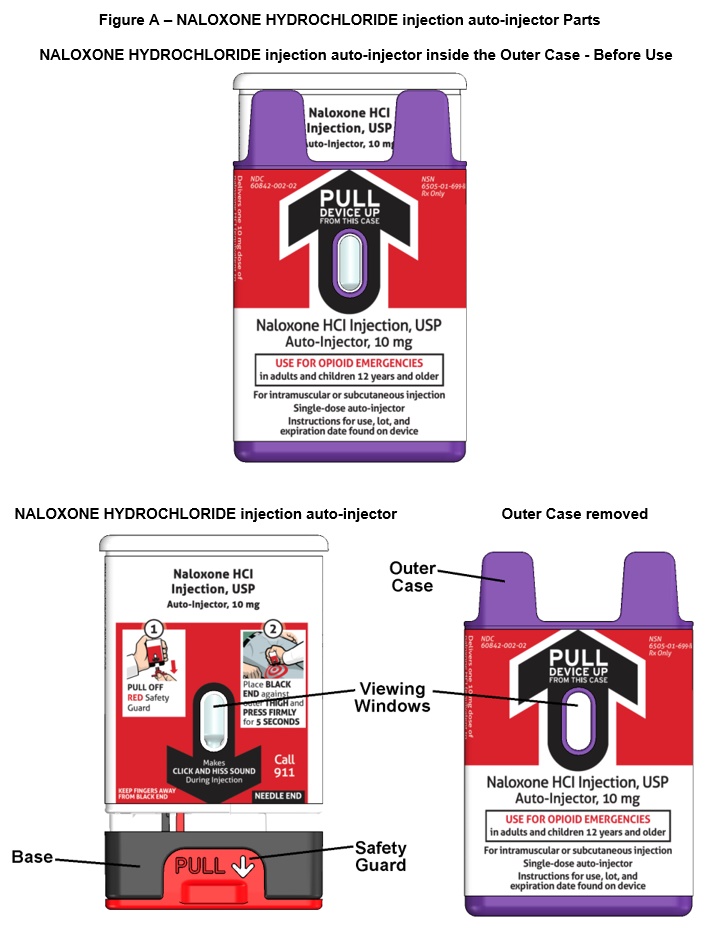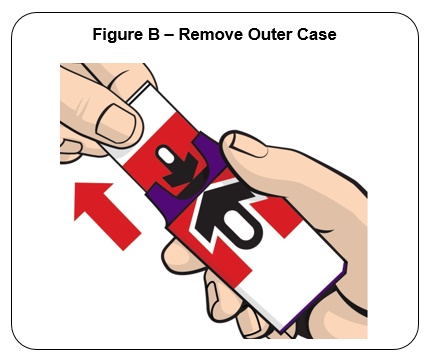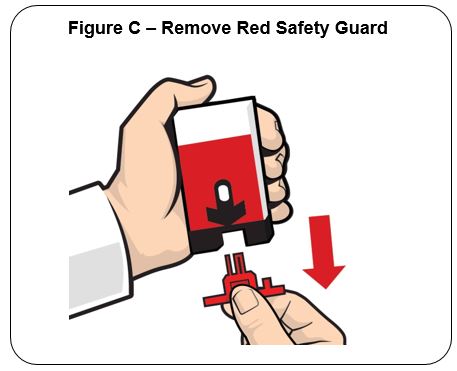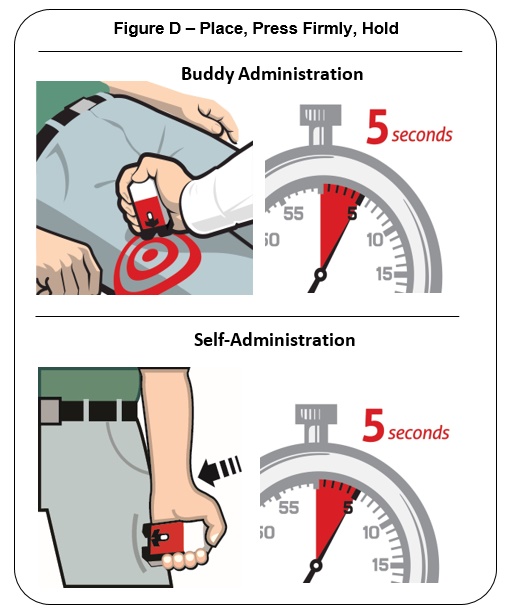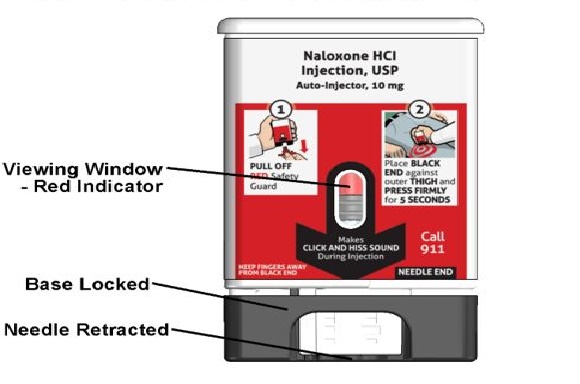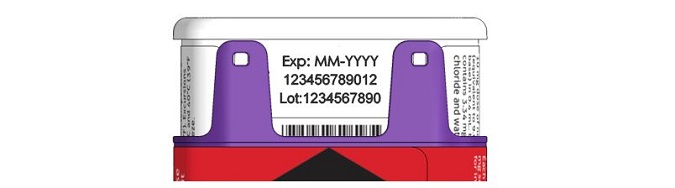 DRUG LABEL: Naloxone Hydrochloride Injection, USP, Auto-Injector
NDC: 60842-002 | Form: INJECTION, SOLUTION
Manufacturer: Kaleo, Inc.
Category: prescription | Type: HUMAN PRESCRIPTION DRUG LABEL
Date: 20220311

ACTIVE INGREDIENTS: NALOXONE HYDROCHLORIDE 10 mg/0.4 mL

HIGHLIGHTS OF PRESCRIBING INFORMATION

These highlights do not include all the information needed to use NALOXONE HYDROCHLORIDE INJECTION safely and effectively. See full prescribing information for NALOXONE HYDROCHLORIDE INJECTION.
NALOXONE HYDROCHLORIDE injection, for intramuscular or subcutaneous use
Initial U.S. Approval: 1971

1 INDICATIONS AND USAGE

NALOXONE HYDROCHLORIDE injection is an opioid antagonist indicated for use by military personnel and chemical incident responders for:

- Emergency treatment of patients 12 years of age and older where use of high-potency opioids such as fentanyl analogues as a chemical weapon is suspected. (1)
- Temporary prophylaxis of respiratory and/or central nervous system depression in military personnel and chemical incident responders entering an area contaminated with high-potency opioids such as fentanyl analogues. (1)

2 DOSAGE AND ADMINISTRATION

- Administer NALOXONE HYDROCHLORIDE injection according to the INSTRUCTIONS FOR USE. (2.1)
- Administer as soon as possible after known or suspected opioid exposure and seek emergency medical assistance immediately after the first dose. (2.1)
- Administer into the anterolateral aspect of the thigh, through clothing if necessary. (2.2)
- If the patient relapses into respiratory or central nervous system depression after the first dose, administer additional naloxone HCl, as necessary, until emergency medical assistance becomes available. (2.2)
- Keep the patient under continued surveillance until medical care is available. (2.2)

3 DOSAGE FORMS AND STRENGTHS

Injection: 10 mg/0.4 mL solution in a single-dose, pre-filled auto-injector. (3)

4 CONTRAINDICATIONS

Hypersensitivity to naloxone hydrochloride or to any of the other ingredients in NALOXONE HYDROCHLORIDE injection. (4)

5 WARNINGS AND PRECAUTIONS

- Precipitation of Severe Opioid Withdrawal: Use in patients who are opioid dependent may cause abrupt opioid withdrawal. Monitor for the development of opioid withdrawal. Use of a product that delivers a dose lower than 10 mg of naloxone HCl may be preferable in treatment of a patient with known opioid dependence. (5.1)
- Risk of Recurrent Respiratory and Central Nervous System Depression: Due to the duration of action of naloxone HCl relative to the opioid, keep the patient under continued surveillance and administer additional naloxone HCl, as necessary, while awaiting emergency medical assistance. (5.2)

6 ADVERSE REACTIONS

The following adverse reactions were observed in more than one subject in clinical studies evaluating NALOXONE HYDROCHLORIDE injection: dizziness, feeling hot, headache, and injection site erythema. (6.1)

To report SUSPECTED ADVERSE REACTIONS, contact kaleo, Inc. at 1-877-341-5330 or FDA at 1-800-FDA-1088 or www.fda.gov/medwatch.

FULL PRESCRIBING INFORMATION

1 INDICATIONS AND USAGE

NALOXONE HYDROCHLORIDE injection is indicated for use by military personnel and chemical incident responders for:

- Emergency treatment of patients 12 years of age and older where use of high-potency opioids such as fentanyl analogues as a chemical weapon is suspected.
- Temporary prophylaxis of respiratory and/or central nervous system depression in military personnel and chemical incident responders entering an area contaminated with high-potency opioids such as fentanyl analogues.

2 DOSAGE AND ADMINISTRATION

2.1 Important Administration Instructions

- Read the Instructions for Use at the time of receiving a single-dose, pre-filled NALOXONE HYDROCHLORIDE injection auto-injector.
- Administer NALOXONE HYDROCHLORIDE injection as soon as possible after known or suspected opioid exposure because prolonged respiratory depression may result in damage to the central nervous system or death.
- NALOXONE HYDROCHLORIDE injection contains 10 mg/0.4 mL naloxone HCl in a single-dose, pre-filled auto-injector for intramuscular or subcutaneous use only.
- Do not attempt to reuse the NALOXONE HYDROCHLORIDE injection auto-injector.
- Periodically visually inspect NALOXONE HYDROCHLORIDE injection through the viewing window for particulate matter. Request a replacement if the solution is cloudy or contains particles, or if the glass container is damaged.
- Once the red safety guard is removed, NALOXONE HYDROCHLORIDE injection auto-injector must be used immediately or disposed of properly. Do not attempt to replace the red safety guard once it is removed.

2.2 Dosing in Adults and Pediatric Patients at Least 12 Years Old

- Inject NALOXONE HYDROCHLORIDE injection into the anterolateral aspect of the thigh according to the Instructions for Use and the printed instructions on the device label.
- In summary,
  - Ensure that the injection site is free of other materials (e.g., equipment or other obstructions), except for clothing.
  - Pull the auto-injector from the outer case.
  - When ready to use, firmly pull off the red safety guard. Do not touch the black base of the auto-injector, which is where the needle comes out.
  - Place the black end of the auto-injector against the anterolateral aspect of the thigh, through clothing, if needed.
  - Press firmly until you hear a click and hiss sound and then hold in place for 5 seconds.
- Upon actuation, the auto-injector automatically inserts the needle intramuscularly or subcutaneously, delivers the naloxone HCl injection, and retracts the needle into the device. The needle will not be visible before, during, or after the injection.
- Post-injection, the black base locks in place and a red indicator appears in the drug viewing window.
- NALOXONE HYDROCHLORIDE injection can be injected through clothing or MOPP4 PPE.
- NALOXONE HYDROCHLORIDE injection can be self- or buddy-administered.

Emergency treatment of patients 12 years of age and older where use of high-potency opioids such as fentanyl analogues as a chemical weapon is suspected.

- Seek immediate emergency medical assistance immediately after administration of the first dose of NALOXONE HYDROCHLORIDE injection.
- Keep the patient under continued surveillance until medical care is available.
- If the patient relapses into respiratory and/or central nervous system depression after the first dose of NALOXONE HYDROCHLORIDE injection, administer additional naloxone HCl, as necessary, until emergency medical assistance becomes available.
- If the patient does not show some improvement after administering the dose of NALOXONE HYDROCHLORIDE injection, consider if the respiratory depression is due to a non-opioid etiology.

Temporary prophylaxis of respiratory and/or central nervous system depression in military personnel and chemical incident responders entering an area contaminated with high-potency opioids such as fentanyl analogues.

- Administer immediately prior to entering an area believed to be contaminated with high-potency opioids.
- Each pre-filled NALOXONE HYDROCHLORIDE injection can only be used one time.
- NALOXONE HYDROCHLORIDE injection provides temporary protection. If exposure to high potency opioids is prolonged, additional doses may be necessary.

3 DOSAGE FORMS AND STRENGTHS

Injection: 10 mg/0.4 mL naloxone HCl solution (equivalent to 9.0 mg naloxone base) in a single-dose pre-filled auto-injector.

4 CONTRAINDICATIONS

NALOXONE HYDROCHLORIDE injection is contraindicated in individuals known to be hypersensitive to naloxone HCl or to any of the other ingredients.

5 WARNINGS AND PRECAUTIONS

5.1 Precipitation of Severe Opioid Withdrawal

The safety of NALOXONE HYDROCHLORIDE injection, 10 mg, in an auto-injector has not been established in opioid-dependent adults. Because NALOXONE HYDROCHLORIDE injection is expected to cause abrupt opioid withdrawal in opioid-dependent individuals, use NALOXONE HYDROCHLORIDE injection when the potential benefits are expected to outweigh the risks. Use of a product that delivers a dose lower than 10 mg naloxone HCl may be preferable in treatment of a patient with known opioid dependence.

Abrupt reversal of opioid depression after using naloxone HCl may result in nausea, vomiting, sweating, tremulousness, tachycardia, hypotension, hypertension, seizures, ventricular tachycardia and fibrillation, pulmonary edema, and cardiac arrest. Death, coma, and encephalopathy have been reported as sequelae of these events. Although a direct cause and effect relationship has not been established, after use of naloxone HCl, monitor individuals with opioid-dependence for hypotension, ventricular tachycardia or fibrillation, and pulmonary edema in an appropriate healthcare setting. It has been suggested that the pathogenesis of pulmonary edema associated with the use of naloxone HCl is similar to neurogenic pulmonary edema, i.e., a centrally mediated massive catecholamine response leading to a dramatic shift of blood volume into the pulmonary vascular bed resulting in increased hydrostatic pressures.

5.2 Risk of Recurrent Respiratory and Central Nervous System Depression

The duration of action of most opioids may exceed that of naloxone HCl resulting in a return of respiratory and/or central nervous system depression after an initial improvement in symptoms. Therefore, it is necessary to seek emergency medical assistance immediately after delivering the first dose of NALOXONE HYDROCHLORIDE injection. Keep the patient under continued surveillance and administer additional naloxone HCl as necessary [see Dosage and Administration (2.2)]. Additional supportive and/or resuscitative measures may be helpful while awaiting emergency medical assistance.

6 ADVERSE REACTIONS

The following serious adverse reactions are discussed elsewhere in the labeling:

- Precipitation of Severe Opioid Withdrawal [see Warnings and Precautions (5.1)]
- Recurrent Respiratory and Central Nervous System Depression [see Warnings and Precautions (5.2)]

6.1 Clinical Trials Experience

Because clinical studies are conducted under widely varying conditions, adverse reaction rates observed in the clinical studies of a drug cannot be directly compared to the rates in the clinical studies of another drug and may not reflect the rates observed in practice.

In three pharmacokinetic studies with a total of 78 healthy adult subjects exposed to NALOXONE HYDROCHLORIDE injection 0.4 mg auto-injector, two NALOXONE HYDROCHLORIDE injection 0.4 mg (0.8 mg naloxone HCl total) auto-injectors, NALOXONE HYDROCHLORIDE injection 2 mg auto-injector, or NALOXONE HYDROCHLORIDE injection 10 mg auto-injector, adverse reactions occurring in more than one subject were dizziness, feeling hot, headache, and injection site erythema.

6.2 Postmarketing Experience

The following adverse reactions have been identified during the use of naloxone HCl to reverse the effects of opioids. Because these reactions are reported voluntarily from a population of uncertain size, it is not always possible to reliably estimate their frequency or establish a causal relationship to drug exposure: aggression, anger, anxiety, back pain, bradycardia, cardiac arrest, confusion, depression, disorientation, dyspnea, hypertension, hypotension, loss of consciousness, malaise, miosis, pain, pulmonary edema, somnolence, unresponsiveness to stimuli, and ventricular tachycardia and fibrillation. Death, coma, and encephalopathy have been reported as sequelae of these events. Excessive doses of naloxone HCl have resulted in significant reversal of analgesia and have caused agitation [see Warnings and Precautions (5.1)].

8 USE IN SPECIFIC POPULATIONS

8.1 Pregnancy

Risk Summary

Life-sustaining therapy for opioid overdose should not be withheld (see Clinical Considerations). There is an absence of data on naloxone HCl administered for known or suspected opioid overdose in pregnant patients. Available data from retrospective cohort studies on oral naloxone use in pregnant women for opioid use disorder have not identified a drug-associated risk of major birth defects, miscarriage, or other adverse maternal or fetal outcomes. In animal reproduction studies, no embryotoxic or teratogenic effects were observed in mice and rats treated with naloxone HCl during the period of organogenesis at doses equivalent to 4-times and 8-times, respectively, the dose of a 50 kg human given 10 mg naloxone HCl [see Data].

The estimated background risk of major birth defects and miscarriage for the indicated population is unknown. All pregnancies have a background risk of birth defect, loss, or other adverse outcomes. In the U.S. general population, the estimated background risk of major birth defects and miscarriage in clinically recognized pregnancies is 2% to 4% and 15% to 20%, respectively.

Clinical Considerations

Disease-associated maternal and/or embryo/fetal risk

An opioid overdose is a medical emergency and can be fatal for the pregnant woman and fetus if left untreated. Treatment with NALOXONE HYDROCHLORIDE injection for opioid overdose should not be withheld because of potential concerns regarding the effects of NALOXONE HYDROCHLORIDE injection on the fetus.

Data

Animal Data

Naloxone HCl was administered during organogenesis to mice and rats at doses 4-times and 8-times, respectively, the dose of 10 mg/day given to a 50 kg human (when based on body surface area or mg/m^2). These studies demonstrated no embryotoxic or teratogenic effects due to naloxone HCl.

8.2 Lactation

Risk Summary

Naloxone is minimally orally available and is unlikely to affect the breastfed infant. There is no information regarding the presence of naloxone in human milk, or the effects of naloxone on the breastfed infant or on milk production. Published studies in lactating women have shown that naloxone does not affect prolactin or oxytocin hormone levels.

8.4 Pediatric Use

The safety and effectiveness of NALOXONE HYDROCHLORIDE injection, 10 mg, in an auto-injector have been established in pediatric patients 12 years of age and older for emergency treatment where use of high-potency opioids such as fentanyl analogues as a chemical weapon is suspected.

Use of NALOXONE HYDROCHLORIDE injection in this age group is supported by evidence from adult bioavailability studies, adult PK/PD modeling and simulation analysis supporting an effective dose, along with additional evidence from the reported safe and effective use of other naloxone HCl products [see Clinical Pharmacology (12.2)]. No pediatric studies were conducted for NALOXONE HYDROCHLORIDE injection.

The safety and effectiveness of NALOXONE HYDROCHLORIDE injection for intramuscular and subcutaneous use have not been established for pediatric patients less than 12 years old. Absorption of naloxone HCl following subcutaneous or intramuscular administration in pediatric patients may be erratic or delayed. Even when the opiate-intoxicated pediatric patient responds appropriately to naloxone HCl injection, the patient must be carefully monitored for at least 24 hours as a relapse may occur as naloxone is metabolized.

In opioid-dependent pediatric patients, administration of naloxone HCl may result in an abrupt and complete reversal of opioid effects, precipitating an acute opioid withdrawal syndrome. In these settings where it may be preferable to avoid the abrupt precipitation of acute opioid withdrawal symptoms, consider use of an alternative naloxone HCl product that can be dosed according to weight and titrated to effect [see Warnings and Precautions (5.1)].

8.5 Geriatric Use

Clinical studies of naloxone HCl did not include sufficient numbers of subjects aged 65 and over to determine whether they respond differently from younger subjects. Other reported clinical experience has not identified differences in responses between the elderly and younger patients.

Geriatric patients have a greater frequency of decreased hepatic, renal, or cardiac function and of concomitant disease or other drug therapy. Therefore, the systemic exposure of naloxone can be higher in these patients.

11 DESCRIPTION

NALOXONE HYDROCHLORIDE injection, USP, for intramuscular or subcutaneous use, is an opioid antagonist in a pre-filled, single-dose auto-injector containing 10 mg of naloxone HCl in 0.4 mL solution. NALOXONE HYDROCHLORIDE injection is not made with natural rubber latex. Chemically, naloxone HCl is the hydrochloride salt of 17-Allyl-4,5α-epoxy-3,14-dihydroxymorphinan-6-one hydrochloride with the following structure:

C19H21NO4HC1

M.W.363.84

Naloxone HCl occurs as a white to slightly off-white powder, and is soluble in water, in dilute acids, and in strong alkali; slightly soluble in alcohol; practically insoluble in ether and in chloroform.

Each 0.4 mL of NALOXONE HYDROCHLORIDE injection contains 10 mg of naloxone HCl (equivalent to 9.0 mg naloxone base), 3.34 mg of sodium chloride, hydrochloric acid to adjust pH, and water for injection. The pH range is 3.0 to 4.5.

12 CLINICAL PHARMACOLOGY

12.1 Mechanism of Action

Naloxone HCl is an opioid antagonist that antagonizes opioid effects by competing for the same receptor sites.

Naloxone HCl reverses the effects of opioids, including respiratory depression, sedation, and hypotension. Also, it can reverse the psychotomimetic and dysphoric effects of agonist-antagonists such as pentazocine.

12.2 Pharmacodynamics

When naloxone HCl is administered intravenously, the onset of action is generally apparent within two minutes. The time to onset of action is shorter for intravenous compared to subcutaneous or intramuscular routes of administration.

The duration of action is dependent upon the dose and route of administration of naloxone HCl.

Simulations based on data from healthy volunteer studies demonstrated that a single 10 mg naloxone HCl dose could improve depressed ventilation induced by morphine, buprenorphine, fentanyl, and carfentanil. The ability to reverse decreased ventilation rate after naloxone HCl treatment was dependent on the administered opioid, amount of opioid, amount of naloxone, and timing of naloxone HCl administration relative to opioid exposure.

12.3 Pharmacokinetics

A pharmacokinetic study using a crossover design was conducted in 24 fasted healthy subjects to evaluate a single 2 mg NALOXONE HYDROCHLORIDE injection (0.4 mL of 5 mg/mL naloxone HCl solution) and a single 10 mg NALOXONE HYDROCHLORIDE injection (0.4 mL of 25 mg/mL naloxone HCl solution) administered to the anterolateral aspect of the thigh. Plasma samples were analyzed for naloxone 12-hours post dose. The pharmacokinetic parameters obtained in this study are shown in Table 1 and the plasma concentration time profiles of naloxone are presented in Figure 1. A slightly greater than 5-fold increase was observed for 10 mg NALOXONE HYDROCHLORIDE injection compared to 2 mg NALOXONE HYDROCHLORIDE injection for the mean pharmacokinetic parameters of Cmax, AUC0-t, and AUC0-inf.

Table 1 Mean Pharmacokinetic Parameters (%CV) for Naloxone Following NALOXONE HYDROCHLORIDE injection Intramuscular/Subcutaneous Administration to Healthy Subjects

Parameter | 2 mg NALOXONE HYDROCHLORIDE injection (N=24) | 10 mg NALOXONE HYDROCHLORIDE injection (N=24)
Tmax (h)† | 0.17 (0.08, 0.67) | 0.26 (0.09, 0.67)
Cmax (ng/mL) | 6.95 (44.8) | 42.0 (49.9)
AUC0-t (ng.h/mL) | 9.22 (14.6) | 51.1 (17.9)
AUC0-inf (ng.h/mL) | 9.25 (14.6) | 51.3 (17.8)
T1/2(h) | 1.46 (11.1) | 1.46 (14.1)
† Tmax reported as median (minimum, maximum)

Figure 1 Mean ± SD Plasma Concentration of Naloxone, (a) 0-8 h and (b) 0-3 h Following Intramuscular/Subcutaneous Administration using NALOXONE HYDROCHLORIDE injection

(a)

(b)

Absorption

The median Tmax for NALOXONE HYDROCHLORIDE injection is 15.6 minutes (range 5.4 to 40.2 minutes).

Distribution

Following parenteral administration, naloxone is distributed in the body and readily crosses the placenta. Plasma protein binding occurs but is relatively weak. Plasma albumin is the major binding constituent, but significant binding of naloxone also occurs to plasma constituents other than albumin. It is not known whether naloxone is excreted into human milk.

Elimination

The mean plasma half-life of naloxone in healthy adults was 1.46 hours (14.1%CV) following a single administration of NALOXONE HYDROCHLORIDE injection.

Metabolism

Naloxone HCl is metabolized in the liver, primarily by glucuronide conjugation with naloxone-3-glucoronide as the major metabolite.

Excretion

After an oral or intravenous dose, about 25-40% of naloxone is excreted as metabolites in urine within 6 hours, about 50% in 24 hours, and 60-70% in 72 hours.

13 NONCLINICAL TOXICOLOGY

13.1 Carcinogenesis, Mutagenesis, Impairment of Fertility

Carcinogenesis

Long-term animal studies to evaluate the carcinogenic potential of naloxone have not been completed.

Mutagenesis

Naloxone was weakly positive in the Ames mutagenicity and in the in vitro human lymphocyte chromosome aberration test but was negative in the in vitro Chinese hamster V79 cell HGPRT mutagenicity assay and in the in vivo rat bone marrow chromosome aberration study.

Impairment of Fertility

Reproduction studies conducted in mice and rats at doses 4-times and 8-times, respectively, the dose of a 50 kg human given 10 mg/day (when based on surface area or mg/m^2), demonstrated no adverse effect of naloxone HCl on fertility.

16 HOW SUPPLIED/STORAGE AND HANDLING

16.1 How Supplied

NALOXONE HYDROCHLORIDE injection, a colorless to yellow solution of 10 mg/0.4 mL naloxone HCl, provided as follows:

NDC 60842-002-02: Package containing ten single-dose 10 mg/0.4 mL auto-injectors

16.2 Storage and Handling

Storage and Shipping

Store at controlled room temperature 15°C - 25°C (59°F - 77°F); excursions permitted between 4°C and 40°C (39°F and 104°F). Do not freeze. Protect from heat.

Use and Handling

Store the NALOXONE HYDROCHLORIDE injection auto-injector in the outer case provided.

If NALOXONE HYDROCHLORIDE injection is frozen and is needed in an emergency, do NOT wait for NALOXONE HYDROCHLORIDE injection to thaw; get emergency medical help right away. Once thawed, NALOXONE HYDROCHLORIDE injection may be used.

Manufactured for:
Kaleo, Inc.
Richmond, VA 23219

This product may be covered by one or more U.S. patents or pending patent applications. See www.kaleopharma.com/pat for details.

INSTRUCTIONS FOR USE

NALOXONE HYDROCHLORIDE injection (Nuh-laak-sown hai-drow-klaw-ride)
for intramuscular or subcutaneous use

Read the Instructions for Use that comes with NALOXONE HYDROCHLORIDE injection before using it.

NALOXONE HYDROCHLORIDE injection comes in a single-dose, pre-filled auto-injector.

NALOXONE HYDROCHLORIDE injection is indicated for use by military personnel and chemical incident responders for:

- Emergency treatment of people 12 years of age and older where use of high-potency opioids such as fentanyl analogues as a chemical weapon is suspected.
- Temporary prevention (prophylaxis) of either breathing problems (respiratory depression), decreased brain and nerve function (central nervous system depression), or both in military personnel and chemical incident responders entering an area contaminated with high-potency opioids such as fentanyl analogues.

Important:

- Administer NALOXONE HYDROCHLORIDE injection as soon as possible after known or suspected opioid exposure.
- If an individual is unresponsive and opioid exposure is suspected, administer NALOXONE HYDROCHLORIDE injection as quickly as possible because an opioid emergency can cause severe injury or death.
- Each NALOXONE HYDROCHLORIDE injection auto-injector can only be used 1 time.

You do not need to assemble your auto-injector. It comes already assembled for use.

Figure A – NALOXONE HYDROCHLORIDE injection auto-injector Parts

Important note: Before you use the NALOXONE HYDROCHLORIDE injection auto-injector, look at the viewing window. Do not use the auto-injector if the medicine is cloudy or contains particles or if there is a red indicator in the viewing window. Use a new NALOXONE HYDROCHLORIDE injection auto-injector.

How to use the auto-injector:

Step 1.

Firmly pull the auto-injector from the outer case. See Figure B .

Do not go to Step 2 (Do not remove the Red safety guard) until you are ready to use the auto-injector. If you are not ready to use the auto-injector, put it back in the outer case for later use.

If NALOXONE HYDROCHLORIDE injection auto-injector is frozen, do not wait for it to thaw. Use another auto-injector if available. If another auto-injector is not available, get emergency medical help right away.

NALOXONE HYDROCHLORIDE injection auto-injector may still be used if it has been thawed after being previously frozen.

Step 2.

Pull off the Red safety guard. See Figure C .

To reduce the chance of an accidental injection, do not touch the Black base of the auto-injector, which is where the needle comes out

Note: The Red safety guard is made to fit tightly. Pull firmly to remove.

Do not replace the Red safety guard after it is removed.

Step 3.

Place the Black end of the auto-injector against the outer thigh, through clothing or personal protective equipment (including MOPP4 PPE), if needed. Make sure that the injection site is free of other materials such as equipment or other obstructions, except for clothing. NALOXONE HYDROCHLORIDE injection auto-injector may be self-administered or administered by a buddy.

Press firmly until you hear a click and hiss sound and then hold in place for 5 seconds. See Figure D .

Note: The auto-injector makes a distinct sound (click and hiss) when it is pressed against the thigh. The click and hiss indicates the start of the injection. This is normal and means that the auto-injector is working correctly. Keep the auto-injector firmly pressed against the thigh for 5 seconds after you hear the click and hiss sound. After the medicine is injected, the needle will retract back up into the auto-injector and is not visible after use.

Step 4.

After administering the first dose of NALOXONE HYDROCHLORIDE injection, get emergency medical help right away.

Rescue breathing or CPR (cardiopulmonary resuscitation) may be given while waiting for emergency medical help. If there is no response to NALOXONE HYDROCHLORIDE injection consider if respiratory depression is caused by something other than opioid exposure. Watch the person closely. If symptoms return, additional naloxone may be administered.

You may need additional doses of NALOXONE HYDROCHLORIDE injection if you are being exposed to high-potency opioids for an extended period of time. NALOXONE HYDROCHLORIDE injection auto-injector provides temporary protection against opioid exposure.

How to know that the auto-injector has been used.. See Figure E .

- The viewing window will no longer be clear. You will see a Red indicator.
- The Black base will lock into place.

Figure E - NALOXONE HYDROCHLORIDE injection auto-injector – After Use

What to do after the auto-injector has been used:

- Get emergency medical help right away.
- The auto-injector cannot be reused. Put the auto-injector back in the outer case after it has been used.
- Do not throw away the auto-injector in the trash. Do not recycle the auto-injector.
- The auto-injector must be properly disposed of in a sharps container.

There may be local or state laws about how to throw away used auto-injectors.

How should I store NALOXONE HYDROCHLORIDE injection?

- Store NALOXONE HYDROCHLORIDE injection auto-injector at room temperature between 59°F to 77°F (15°C to 25°C). Storage temperature excursions permitted between 39°F to 104°F (4°C to 40°C).
- Protect from heat and do not freeze.
- Keep the NALOXONE HYDROCHLORIDE injection auto-injector in its outer case until ready to use.
- Occasionally check the viewing window of the NALOXONE HYDROCHLORIDE injection auto-injector. If the medicine is cloudy, contains particles, or if the glass container is damaged, replace the auto-injector with a new one.
- NALOXONE HYDROCHLORIDE injection auto-injector has an expiration date. See Figure F . Replace it before the expiration date.

Figure F – Expiration Date Located on Back of the NALOXONE HYDROCHLORIDE injection auto-injector

Keep NALOXONE HYDROCHLORIDE injection and all medicines out of the reach of children.

This Instructions for Use has been approved by the U.S. Food and Drug Administration.

Manufactured for: Kaleo, Inc., Richmond, VA 23219
Issued: 02/2022